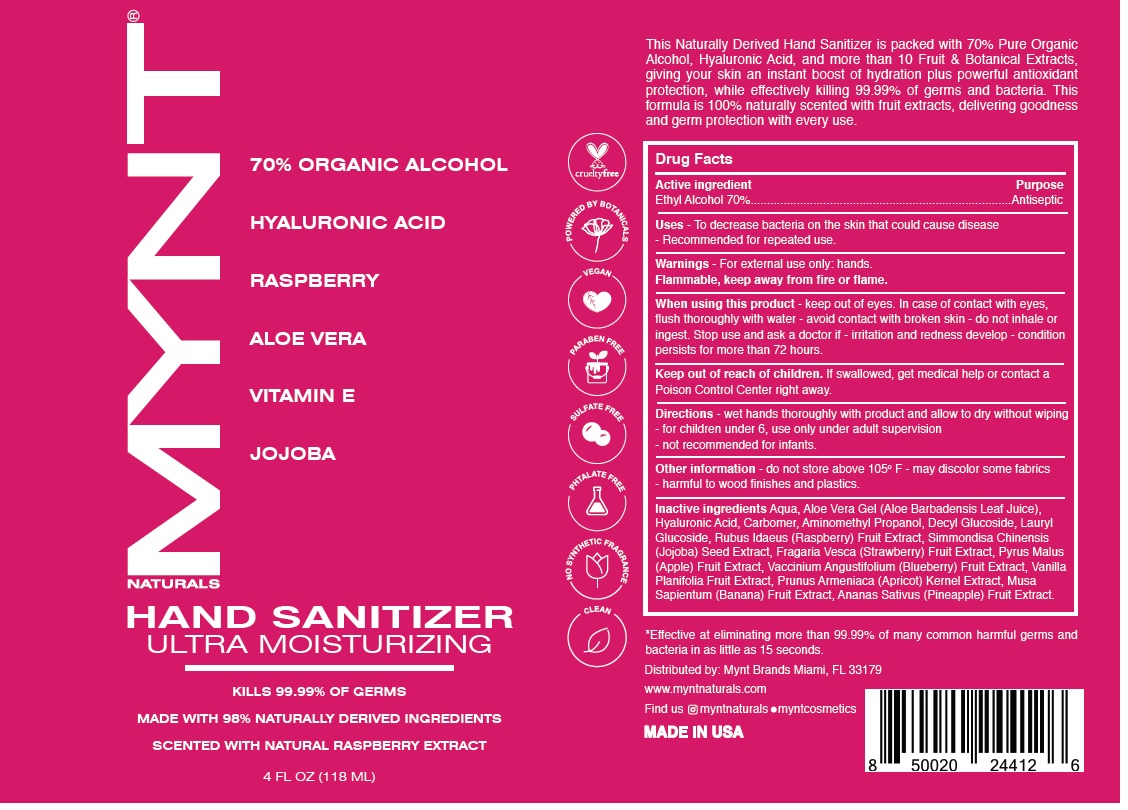 DRUG LABEL: MYNT NATURALS SCENTED HAND SANITIZER RASPBERRY
NDC: 79442-102 | Form: GEL
Manufacturer: Prive International Inc.
Category: otc | Type: HUMAN OTC DRUG LABEL
Date: 20200930

ACTIVE INGREDIENTS: ALCOHOL 70 mL/100 mL
INACTIVE INGREDIENTS: WATER; ALOE VERA LEAF; HYALURONIC ACID; CARBOMER HOMOPOLYMER, UNSPECIFIED TYPE; AMINOMETHYLPROPANOL; DECYL GLUCOSIDE; LAURYL GLUCOSIDE; RASPBERRY; SIMMONDSIA CHINENSIS SEED; FRAGARIA VESCA FRUIT; APPLE; LOWBUSH BLUEBERRY; VANILLA BEAN; PRUNUS ARMENIACA SEED; BANANA; PINEAPPLE

MYNT® NATURALS HAND SANITIZER SCENTED WITH NATURAL RASPBERRY EXTRACT

Active ingredient

Ethyl Alcohol 70%

Purpose

Antiseptic

INDICATIONS AND USAGE

Uses - To decrease bacteria on the skin that could cause disease - Recommended for repeated use.

Warnings - For external use only: hands.

Flammable, keep away from fire or flame.

When using this product - keep out of eyes. In case of contact with eyes, flush thoroughly with water - avoid contact with broken skin - do not inhale or ingest. Stop use and ask a doctor if - irritation and redness develop - condition persists for more than 72 hours.

Keep out of reach of children. If swallowed, get medical help or contact a Poison Control Center right away.

DOSAGE AND ADMINISTRATION

Directions - wet hands thoroughly with product and allow to dry without wiping - for children under 6, use only under adult supervision - not recommended for infants.

Other information - do not store above 105° F - may discolor some fabrics - harmful to wood finishes and plastics.

INACTIVE INGREDIENT

Inactive ingredients Aqua, Aloe Vera Gel (Aloe Barbadensis Leaf Juice), Hyaluronic Acid, Carbomer, Aminomethyl Propanol, Decyl Glucoside, Lauryl Glucoside, Rubus Idaeus (Raspberry) Fruit Extract, Simmondisa Chinensis (Jojoba) Seed Extract, Fragaria Vesca (Strawberry) Fruit Extract, Pyrus Malus (Apple) Fruit Extract, Vaccinium Angustifolium (Blueberry) Fruit Extract, Vanilla Planifolia Fruit Extract, Prunus Armeniaca (Apricot) Kernel Extract, Musa Sapientum (Banana) Fruit Extract, Ananas Sativus (Pineapple) Fruit Extract.

70% ORGANIC ALCOHOL

HYALURONIC ACID

RASPBERRY

ALOE VERA

VITAMIN E

JOJOBA

ULTRA MOISTURIZING

KILLS 99.99% OF GERMS

MADE WITH 98% NATURALLY DERIVED INGREDIENTS

SCENTED WITH NATURAL RASPBERRY EXTRACT

cruelty free

POWERED BY BOTANICALS

VEGAN

PARABEN FREE

SULFATE FREE

PHTALATE FREE

NO SYNTHETIC FRAGRANCE

CLEAN

This Naturally Derived Hand Sanitizer is packed with 70% Pure Organic Alcohol, Hyaluronic Acid, and more than 10 Fruit & Botanical Extracts, giving your skin an instant boost of hydration plus powerful antioxidant protection, while effectively killing 99.99% of germs and bacteria. This formula is 100% naturally scented with fruit extracts, delivering goodness and germ protection with every use.

*Effective at eliminating more than 99.99% of many common harmful germs and bacteria in as little as 15 seconds.

Distributed by: Mynt Brands Miami, FL 33179

www.myntnaturals.com

Find us myntnaturals • myntcosmetics

MADE IN USA